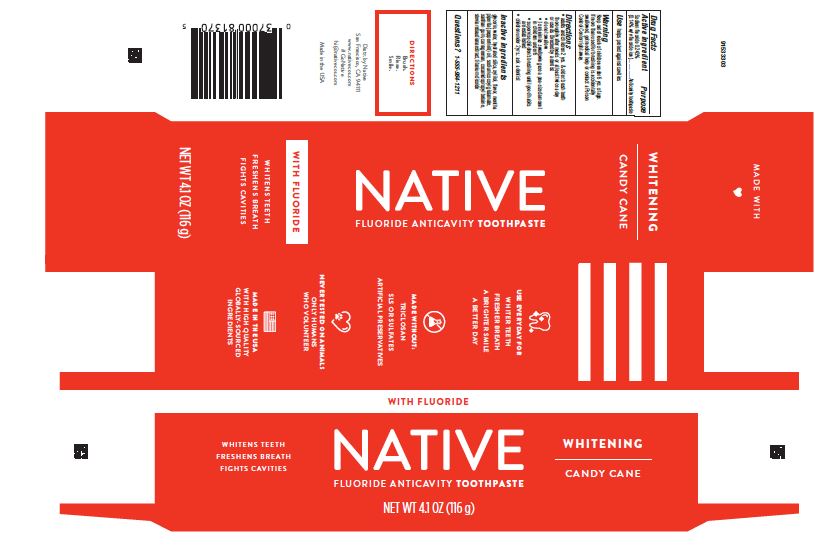 DRUG LABEL: Native
NDC: 69423-947 | Form: PASTE, DENTIFRICE
Manufacturer: Procter & Gamble Manufacturing Company
Category: otc | Type: HUMAN OTC DRUG LABEL
Date: 20250806

ACTIVE INGREDIENTS: SODIUM FLUORIDE 1.4 mg/1 g
INACTIVE INGREDIENTS: TITANIUM DIOXIDE; CARRAGEENAN; XANTHAN GUM; WATER; HYDRATED SILICA; GLYCERIN; STEVIA REBAUDIANA WHOLE; SODIUM COCOYL GLUTAMATE; COCAMIDOPROPYL BETAINE; XYLITOL; PEPPERMINT OIL

Native Whitening Candy Cane

Drug Facts

Active ingredient

Sodium fluoride 0.243% (0.14% w/v fluoride ion)

Purpose

Anticavity toothpaste

Use

helps protect against cavities

Warnings

Keep out of reach of children under 6 yrs of age. If more than used for brushing is accidentally swallowed, get medical help or contact a Poison Control Center right away.

Directions

- adults and children 2 yrs. & older: brush teeth thoroughly after meals or at least twice a day or use as directed by a dentist
- do not swallow
- to minimize swallowing use a pea-sized amount in children under 6
- supervise children’s brushing until good habits are established
- children under 2 yrs.: ask a dentist

Inactive ingredients

glycerin, water, hydrated silica, xylitol, flavor, mentha piperita (peppermint) oil, sodium cocoyl glutamate, xanthan gum, carrageenan, cocamidopropyl betaine, stevia rebaudiana extract, titanium dioxide

Questions?

1-888-964-1211

Distr. by Native

San Francisco, CA 94111

PRINCIPAL DISPLAY PANEL - 116 g tube in carton

WITH FLUORIDE

WHITENS TEETH

FRESHENS BREATH

FIGHTS CAVITIES

NATIVE

FLUORIDE ANTICAVITY TOOTHPASTE

WHITENING

CANDY CANE

NET WT 4.1 OZ (116 g)